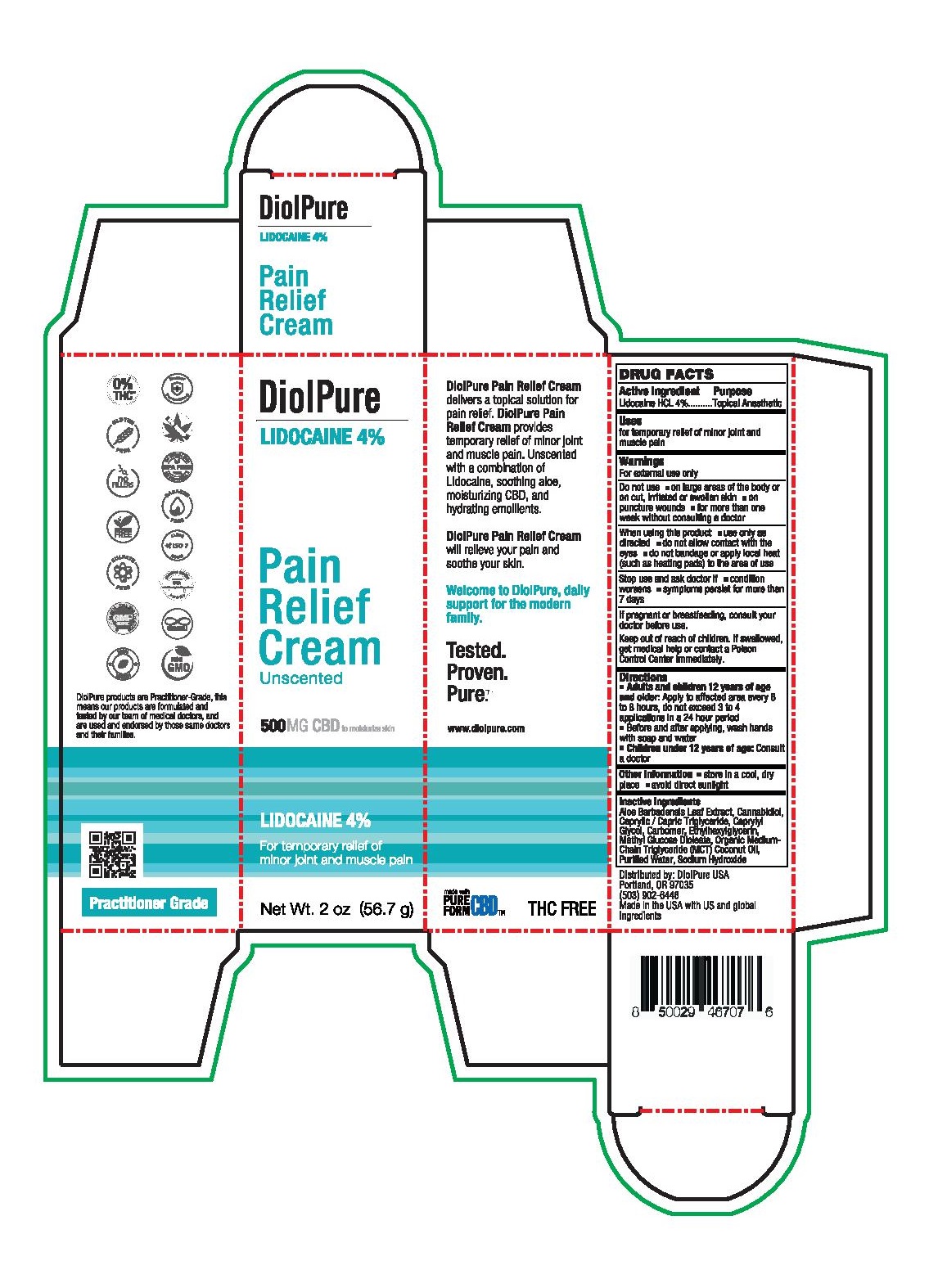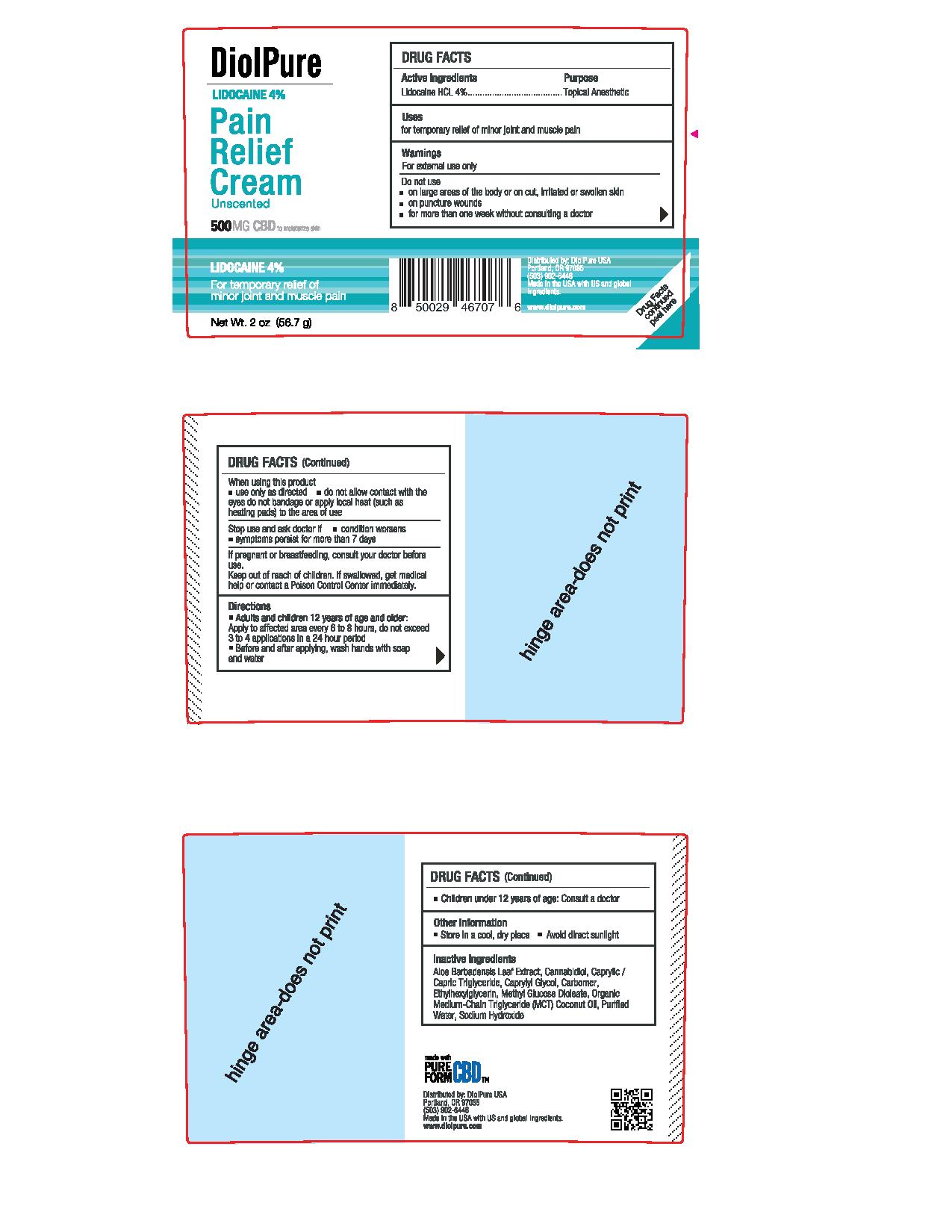 DRUG LABEL: DiolPure Lidocaine Pain Relief Cream
NDC: 82093-002 | Form: CREAM
Manufacturer: DiolPure, LLC
Category: otc | Type: HUMAN OTC DRUG LABEL
Date: 20210709

ACTIVE INGREDIENTS: LIDOCAINE 4 g/100 g
INACTIVE INGREDIENTS: CAPRYLYL GLYCOL; CANNABIDIOL; WATER; COCONUT OIL; SODIUM HYDROXIDE; MEDIUM-CHAIN TRIGLYCERIDES; CARBOMER HOMOPOLYMER, UNSPECIFIED TYPE; METHYL GLUCOSE DIOLEATE; ALOE VERA LEAF; ETHYLHEXYLGLYCERIN

DiolPure Lidocaine Pain Relief Cream

Active ingredient

Lidocaine HCL 4%

Purpose

Lidocaine HCL 4%.................Topical Anesthetic

Uses

for temporary relief of minor joint and muscle pain

Warnings

For external use only

Do not use

- on large areas of the body or on cut, irritated or swollen skin
- on puncture wounds
- for more than one week without consulting a doctor

When using this product

- use only as directed
- do not allow contact with the eyes
- do not bandage or apply local heat (such as heating pads) to the area of use

Stop use and ask doctor if

- condition worsens
- symptoms persist for more than 7 days

PREGNANCY OR BREAST FEEDING

If pregnant or breastfeeding, consult your doctor before use.

Keep out of reach of children. If swallowed, get medical help or contact a Poison Control Center immediately.

Directions

- Adults and children 12 years of age and older: Apply to affected area every 6 to 8 hours, do not exceed 3 to 4 applications in a 24 hour period
- Before and after applying, wash hands with soap and water
- Children under 12 years of age: Consult a doctor

Other information

- store in a cool, dry place
- avoid direct sunlight

Inactive ingredients

Aloe Barbadensis Leaf Extract, Cannabidiol, Caprylic/Capric Triglyceride, Caprylyl Glycol, Carbomer, Ethylhexylglycerin, Methyl Glucose Dioleate, Organic Medium-Chain Triglyceride (MCT), Coconut Oil, Purified Water, Sodium Hydroxide

PACKAGE LABEL

DiolPure

Lidocaine 4%

Pain Relief Cream

Uscented

500MG CBD to moisturize skin

Lidocaine 4%

For temporary relief of minor joint and muscle pain

Net Wt. 2 oz (56.7 g)